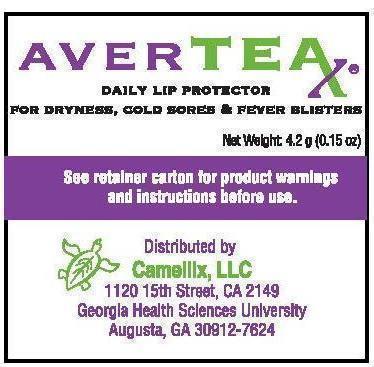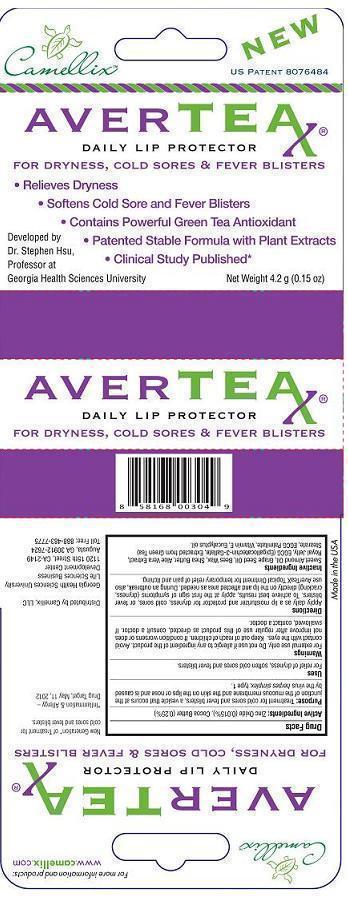 DRUG LABEL: AVERTEAX
NDC: 54866-003 | Form: OINTMENT
Manufacturer: Camellix, LLC
Category: otc | Type: HUMAN OTC DRUG LABEL
Date: 20140308

ACTIVE INGREDIENTS: ZINC OXIDE 0.15 mg/1 g; COCOA BUTTER 2.5 mg/1 g
INACTIVE INGREDIENTS: ALMOND OIL; GRAPE SEED OIL; YELLOW WAX; SHEA BUTTER; ALOE VERA LEAF; Royal Jelly; EPIGALLOCATECHIN GALLATE STEARATES; EPIGALLOCATECHIN GALLATE PALMITATES; .ALPHA.-TOCOPHEROL; EUCALYPTUS OIL

AVERTEX Zinc Oxide & Cocoa Butter

Active ingredient Purpose
Zinc Oxide (0.015%) Cold Sores & Fever blisters
Cocoa Butter(0.25%) Cold Sores & Fever blisters

PURPOSE:

Treatment for cold sores and fever blisters, a vesicle that occurs at the junction of the mucous membrane and the skin on the lips or nose and is caused by the virus herpes simplex, type 1.

ASK DOCTOR:

If condition worsens or does not improve after regular use of the product as directed, consult a doctor.

If swallowed, contact a doctor.

WARNINGS:

For external use only.

DIRECTIONS:

Apply daily as a lip moisturizer and protector for dryness, cold sores, or fever blisters. To achieve best results, apply at the first sign of symptoms (dryness, cracking) directly on the lip and affected area as needed.

OTHER INFORMATION:

During an outbreak, also use AverTeaX Topical Ointment for temporary relief of pain and itching.

STOP USE IF:

Do not use if allergic to any ingredient of the product.

If condition worsens or does not improve after regular use of the product as directed, consult a doctor. If swallowed, contact a doctor.

INDICATIONS & USAGE:

Indications are for relief of dryness, cold sores and fever blisters.

For relief of dryness, soften cold sores and fever blisters.

DO NOT USE:

If allergic to any ingredient of the product.

KEEP OUT OF REACH OF CHILDREN:

- If swallowed, contact a doctor.

INACTIVE INGREDIENT:

Sweet Almond Oil, Grape Seed Oil, Bees Wax, Shea Butter, Aloe Vera Extract, Royal Jelly, EGCG (Epigallocatechin-3-Gallate, Extracted from Green Tea) Stearate, EGCG Palmitate, Vitamin E, Eucalyptus oil.

PACKAGE LABEL

AVERTEAX DAILY LIP PROTECTOR FOR DRYNESS, COLD SORES & FEVER BLISTERS DISTRIBUTED BY CAMELLIX MADE IN USA